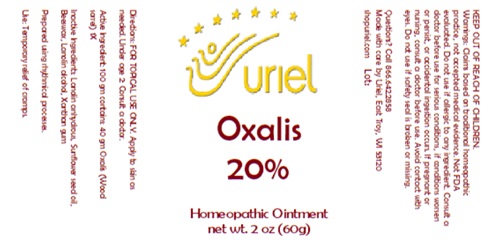 DRUG LABEL: Oxalis 20%
NDC: 48951-7221 | Form: OINTMENT
Manufacturer: Uriel Pharmcy, Inc
Category: homeopathic | Type: HUMAN OTC DRUG LABEL
Date: 20250801

ACTIVE INGREDIENTS: OXALIS STRICTA WHOLE 1 [hp_X]/1 g
INACTIVE INGREDIENTS: LANOLIN ALCOHOL; YELLOW WAX; LANOLIN; XANTHAN GUM; SUNFLOWER OIL

Oxalis 20%

INDICATIONS AND USAGE

Directions: FOR TOPICAL USE ONLY.

DOSAGE AND ADMINISTRATION

Apply to skin as needed. Under age 2: Consult a doctor.

Active Ingredient: 100 gm contains: 40 gm Oxalis (Wood
sorrel) 1X

INACTIVE INGREDIENT

Inactive Ingredients: Lanolin anhydrous, Sunflower seed oil, Beeswax, Lanolin alcohol, Xanthan gum

Prepared using rhythmical processes.

PURPOSE

Use: Temporary relief of cramps.

KEEP OUT OF REACH OF CHILDREN.

WARNINGS

Warnings: Claims based on traditional homeopathic practice, not accepted medical evidence. Not FDA evaluated. Do not use if allergic to any ingredient. Consult a doctor before use for serious conditions, if conditions worsen or persist, or accidental ingestion occurs. If pregnant or nursing, consult a doctor before use. Avoid contact with eyes. Do not use if safety seal is broken or missing.

Questions? Call 866.642.2858
Made with care by Uriel, East Troy, WI 53120
shopuriel.com Lot: